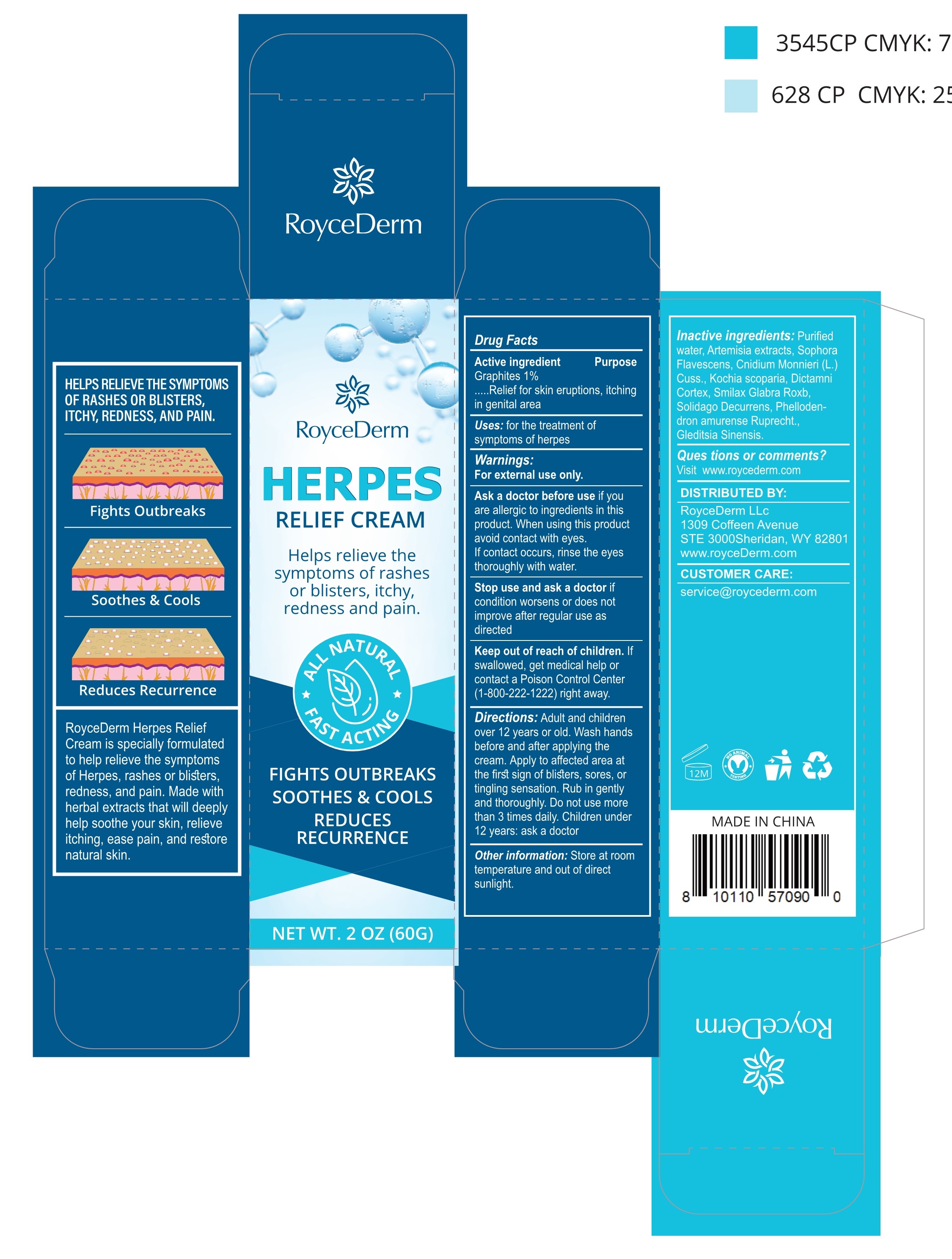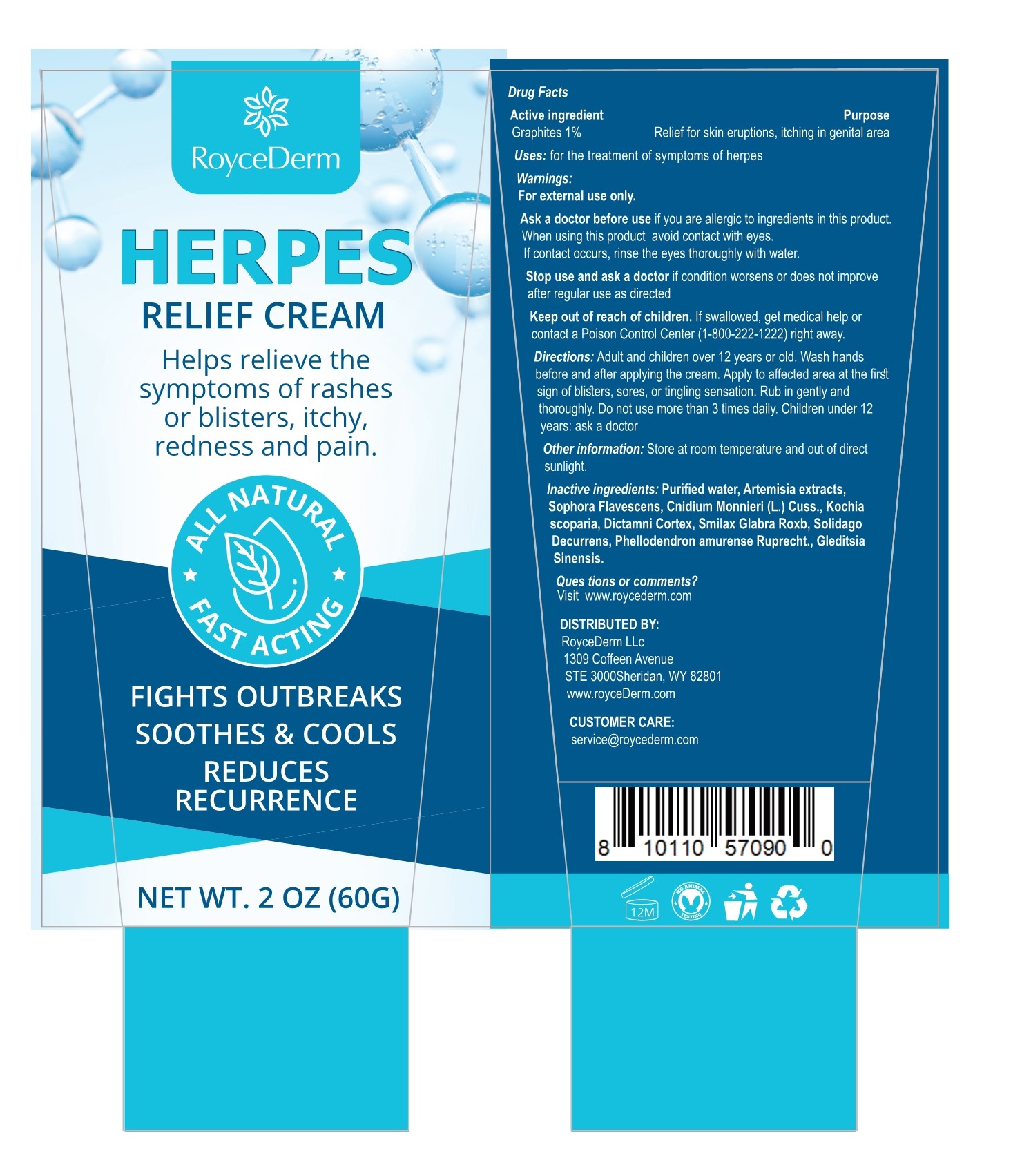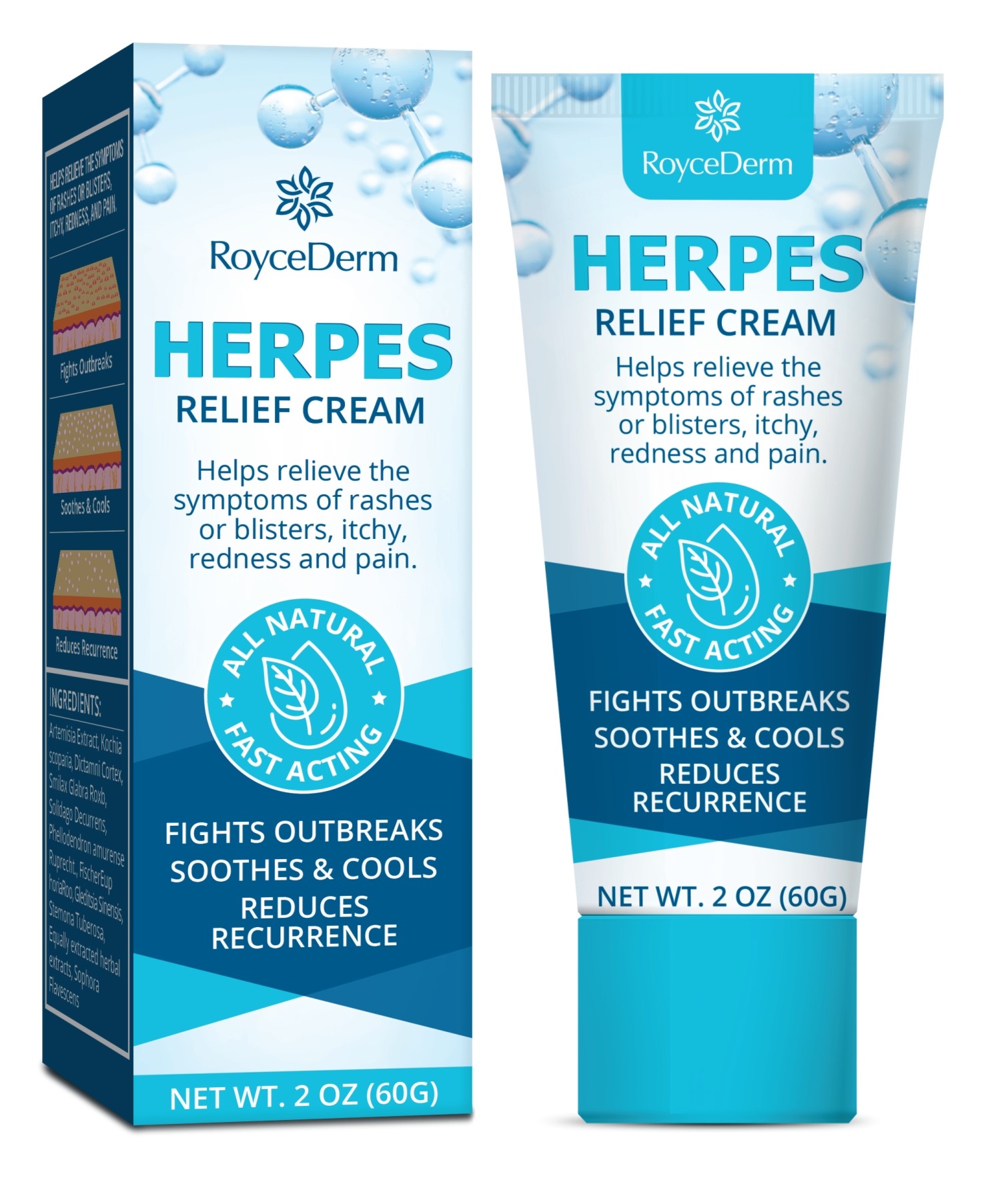 DRUG LABEL: Seborrheic Dermatitis and Psoriasis
NDC: 81799-007 | Form: SHAMPOO
Manufacturer: Ehy Holdings LLC
Category: otc | Type: HUMAN OTC DRUG LABEL
Date: 20230112

ACTIVE INGREDIENTS: WORMWOOD 3 mg/100 mL
INACTIVE INGREDIENTS: DICTAMNUS DASYCARPUS ROOT; WATER; SMILAX GLABRA WHOLE; CNIDIUM MONNIERI FRUIT; BASSIA SCOPARIA POLLEN; SOPHORA FLAVESCENS ROOT

81799-007
Seborrheic Dermatitis & Psoriasis Shampoo

Active Ingredient(s)

ARTEMISIA EXTRACT 【FHFI】3%

Purpose

Seborrheic

Use

Relieves and helps preventrecurrence of scalp: itching, flakingscaling, redness, and irritationassociated with psoriasis andseborrheic dermatitis.

Warnings

For external use only

Do not use morethan 3 times daily. Children under12 years: ask a doctor

When using this productavoid contact with eyes.

STOP USE

condition worsens or does notimprove after regular use asdirected

KEEP OUT OF REACH OF CHILDREN

lf swallowed, get medical help orcontact a Poison Control Center (1-800-222-1222) right away.

Directions

Adult and children over 12 vears or old. Wash handsbefore and after applying the cream. Apply to affected area at the firstsign of blisters, sores, or tingling sensation. Rub in gently andthoroughly. Do not use more than 3 times daily. Children under 12years: ask a doctor

Other information

Stor at room temperature and out of directsunlight.

Inactive ingredients

Purified water, Artemisia extractsSophora Flavescens, Cnidium Monnieri (L) Cuss., Kochiascoparia, Dictamni Cortex, Smilax Glabra Roxb, SolidagoDecurrens, Phellodendron amurense Ruprecht., GleditsiaSinensis

ASK DOCTOR

than 3 times daily. Children under12 years: ask a doctor

QUESTIONS

Visit www.roycederm.com

Package Label - Principal Display Panel

81799-007-1

1

81799-007-1

2

81799-007-1

3